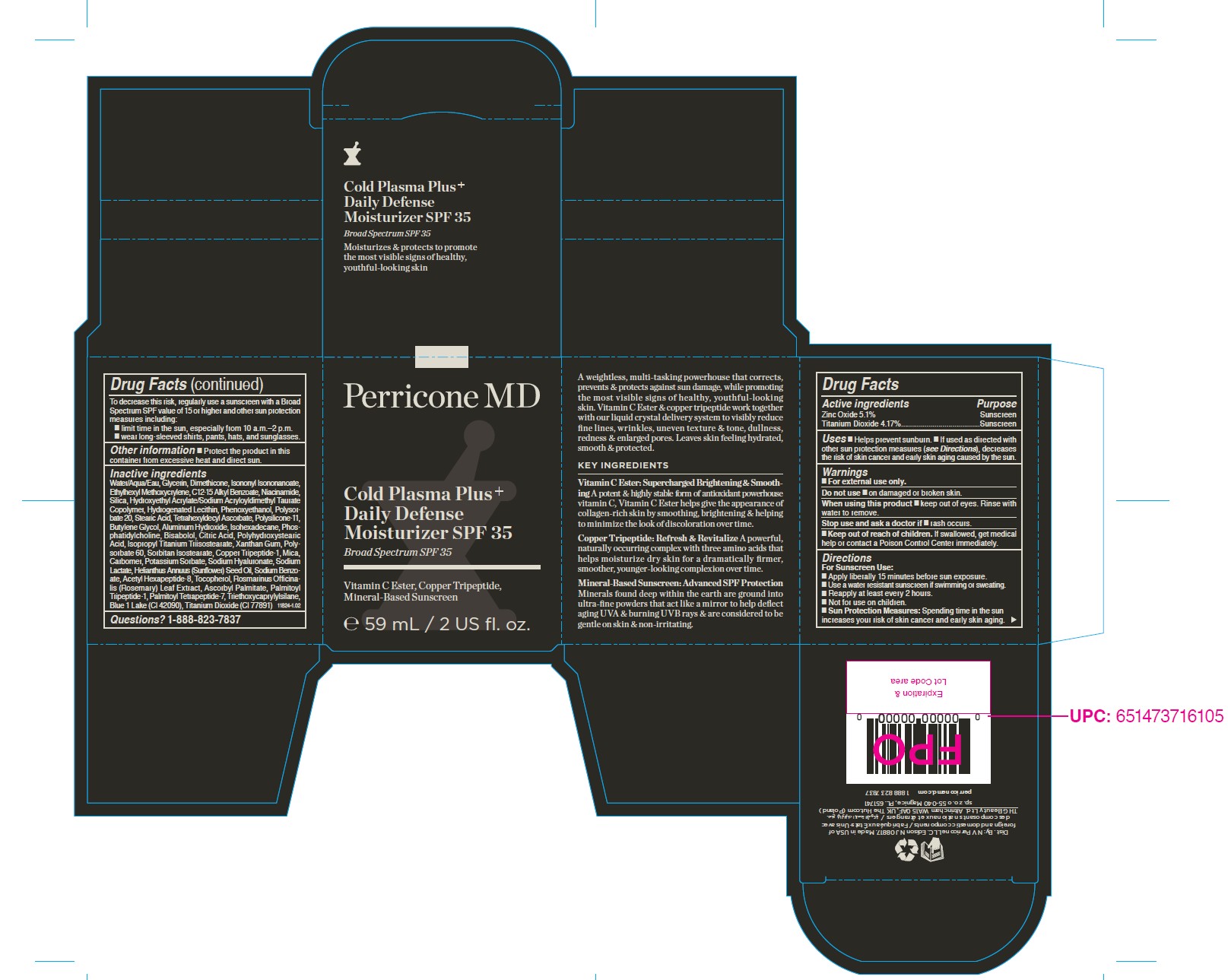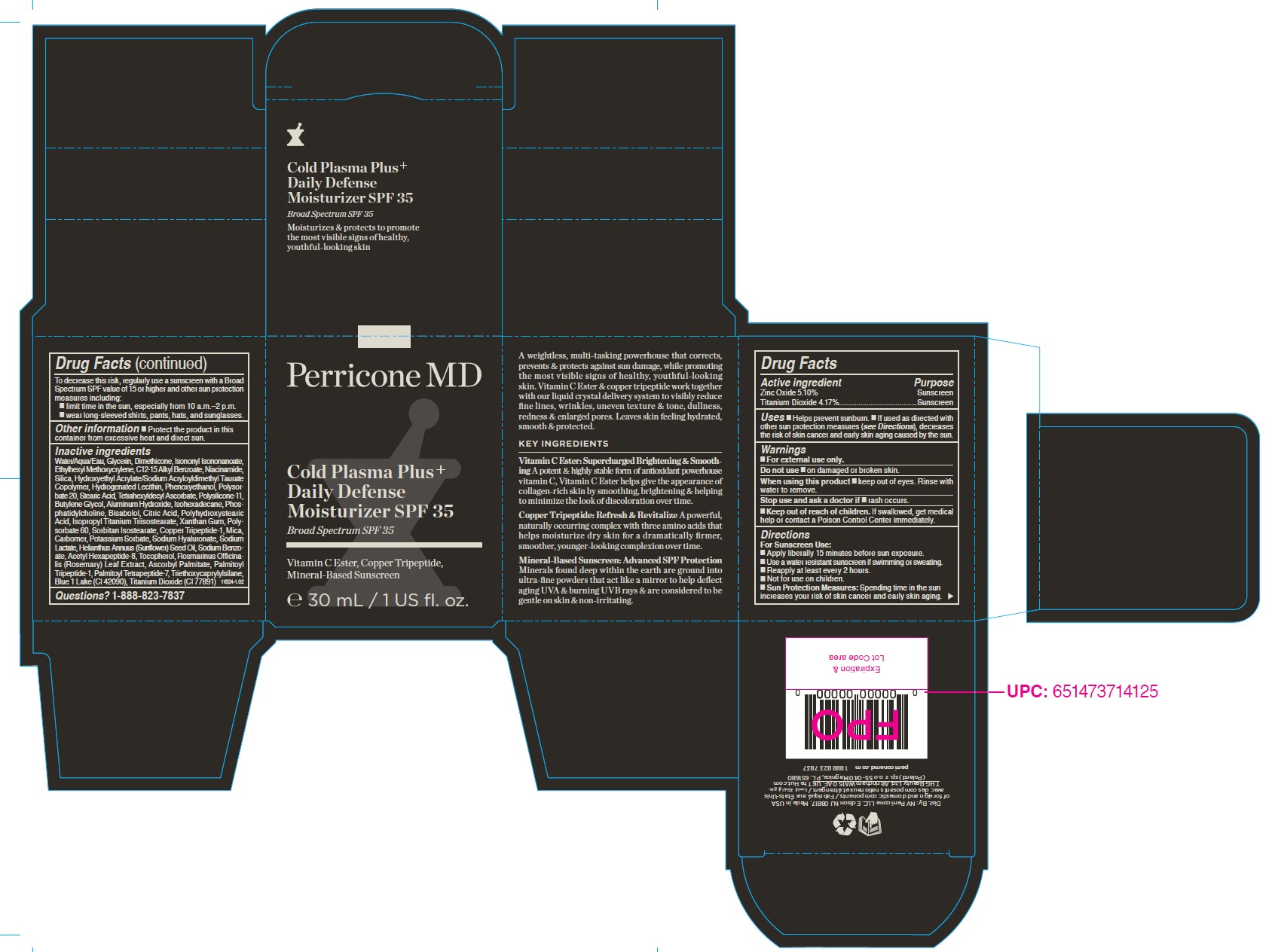 DRUG LABEL: Perricone MD Cold Plasma Plus Daily Defense Moisturizer Broad Spectrum SPF 35
NDC: 84448-519 | Form: CREAM
Manufacturer: THG Beauty USA LLC
Category: otc | Type: HUMAN OTC DRUG LABEL
Date: 20251023

ACTIVE INGREDIENTS: TITANIUM DIOXIDE 4.17 g/100 mL; ZINC OXIDE 5.1 g/100 mL
INACTIVE INGREDIENTS: SORBITAN ISOSTEARATE; SODIUM LACTATE; C12-15 ALKYL BENZOATE; PHENOXYETHANOL; BISABOLOL; ISOPROPYL TITANIUM TRIISOSTEARATE; SODIUM BENZOATE; BLUE 1 LAKE; ALUMINUM HYDROXIDE; HYDROGENATED SOYBEAN LECITHIN; POLYHYDROXYSTEARIC ACID (2300 MW); POLYSORBATE 20; SOYBEAN PHOSPHATIDYLCHOLINE; DIMETHICONE/VINYL DIMETHICONE CROSSPOLYMER (SOFT PARTICLE); WATER; HYDROXYETHYL ACRYLATE/SODIUM ACRYLOYLDIMETHYL TAURATE COPOLYMER (100000 MPA.S AT 1.5%); GLYCERIN; PALMITOYL TETRAPEPTIDE-7; TRIETHOXYCAPRYLYLSILANE; ISONONYL ISONONANOATE; ETHYLHEXYL METHOXYCRYLENE; SILICA; TETRAHEXYLDECYL ASCORBATE; COPPER TRIPEPTIDE-1; ACETYL HEXAPEPTIDE-8; NIACINAMIDE; ISOHEXADECANE; POLYSORBATE 60; MICA; HELIANTHUS ANNUUS (SUNFLOWER) SEED OIL; ASCORBYL PALMITATE; PALMITOYL TRIPEPTIDE-1; ROSEMARY; XANTHAN GUM; SODIUM HYALURONATE; STEARIC ACID; BUTYLENE GLYCOL; CARBOMER; TOCOPHEROL; DIMETHICONE; POTASSIUM SORBATE; CITRIC ACID

ACTIVE INGREDIENT

- Zinc Oxide 5.10%
- Titanium Dioxide 4.17%

PURPOSE

- Sunscreen

INDICATIONS AND USAGE

- Helps prevent sunburn.
- If used as directed with other sun protection measures (see Directions), decreases the risk of skin cancer and early skin aging caused by the sun.

WARNINGS

- For external use only.

DO NOT USE

- on damaged or broken skin

WHEN USING

- keep out of eyes. Rinse with water to remove.

- Stop use and ask a doctor if rash occurs

KEEP OUT OF REACH OF CHILDREN

- If swallowed, get medical help or contact a Poison Control Center immediately.

DOSAGE AND ADMINISTRATION

For Sunscreen Use:

- Apply liberally 15 minutes before sun exposure.
- Use a water resistant sunscreen if swimming or sweating.
- Reapply at least every 2 hours.
- Not for use on children.
- Sun Protection Measures: Spending time in the sun increases your risk of skin cancer and early skin aging. To decrease this risk, regularly use a sunscreen with a Broad Spectrum SPF value of 15 or higher and other sun protection measures including:
- limit time in the sun, especially from 10 a.m.–2 p.m.
- wear long-sleeved shirts, pants, hats, and sunglasses

OTHER SAFETY INFORMATION

- Protect the product in this contaner from excessive heat and direct sun.

INACTIVE INGREDIENT

Water/Aqua/Eau, Glycerin, Dimethicone, Isononyl Isononanoate, Ethylhexyl Methoxycrylene, C12-15 Alkyl Benzoate, Niacinamide, Silica, Hydroxyethyl Acrylate/Sodium Acryloyldimethyl Taurate Copolymer, Hydrogenated Lecithin, Phenoxyethanol, Polysorbate 20, Stearic Acid, Tetrahexyldecyl Ascorbate, Polysilicone-11, Butylene Glycol, Aluminum Hydroxide, Isohexadecane, Phosphatidylcholine, Bisabolol, Citric Acid, Polyhydroxystearic Acid, Isopropyl Titanium Triisostearate, Xanthan Gum, Polysorbate 60, Sorbitan Isostearate, Copper Tripeptide-1, Mica, Carbomer, Potassium Sorbate, Sodium Hyaluronate, Sodium Lactate, Helianthus Annuus (Sunflower) Seed Oil, Sodium Benzoate, Acetyl Hexapeptide-8, Tocopherol, Rosmarinus Officinalis (Rosemary) Leaf Extract, Ascorbyl Palmitate, Palmitoyl Tripeptide-1, Palmitoyl Tetrapeptide-7, Triethoxycaprylylsilane, Blue 1 Lake (CI 42090), Titanium Dioxide (CI 77891)

QUESTIONS

- 1-888-823-7837